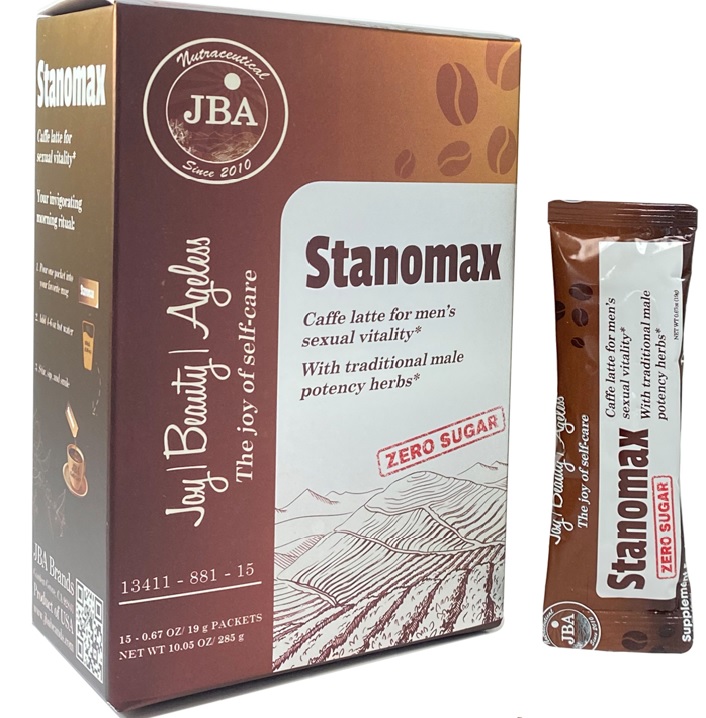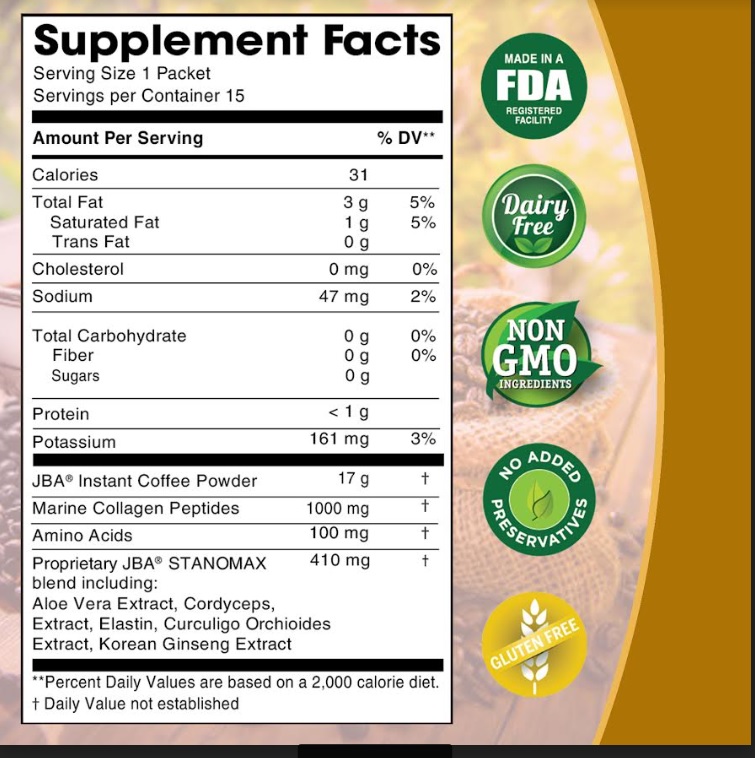 DRUG LABEL: JBA STANOMAX Caffe Latte Zero Sugar
NDC: 13411-881 | Form: POWDER
Manufacturer: Advanced Pharmaceutical Services, Inc. Dba Affordable Quality Pharmaceuticals
Category: other | Type: DIETARY SUPPLEMENT
Date: 20230227

ACTIVE INGREDIENTS: COFFEE BEAN 17 g/19 g; MARINE COLLAGEN, SOLUBLE 1000 mg/19 g; AMINO ACIDS, SOURCE UNSPECIFIED 100 mg/19 g; ALOE VERA LEAF 100 mg/19 g; OPHIOCORDYCEPS SINENSIS 100 mg/19 g; ELASTIN BOVINE 10 mg/19 g; CURCULIGO ORCHIOIDES WHOLE 100 mg/19 g; ASIAN GINSENG 100 mg/19 g

Identity

Dietary supplement

Direction

Your invigorating morning ritual:

- Pour one packet into your favorite mug
- Add 4-6oz hot water
- Stir, sip, and smile

HEALTH CLAIM

JBA® STANOMAX Caffe’ Latte for Men

With traditional male potency herbs*

ZERO SUGAR

Coffee that Does Double Duty
Reawaken your sexual vitality with our delicious Stanomax Caffe Latte.* Made with bold, creamy coffee, strengthening collagen peptides, and traditional Asian male potency herbs, it’s got what you need to rekindle that spark, so you can face the day with vigor and confidence.*

Boost Vitality & Performance*
With dark, rich coffee, a natural stimulant that improves performance and increases healthy blood flow, helping to increase your satisfaction and stamina.*

Keep Tissues Firm & Healthy*
With 1,000 mg marine collagen peptides to help replenish your collagen levels, an important structural protein that makes up a major components of the penis.*

Enhance Desire & Potency*
With traditional Asian herbs such as cordyceps, Korean ginseng, kali musli, and aloe vera, which have been used to support sexual desire and male potency for generations.*

* These statements have not been evaluated by the Food & Drug Administration. This product is not intended to diagnose, treat, cure, or prevent any disease.